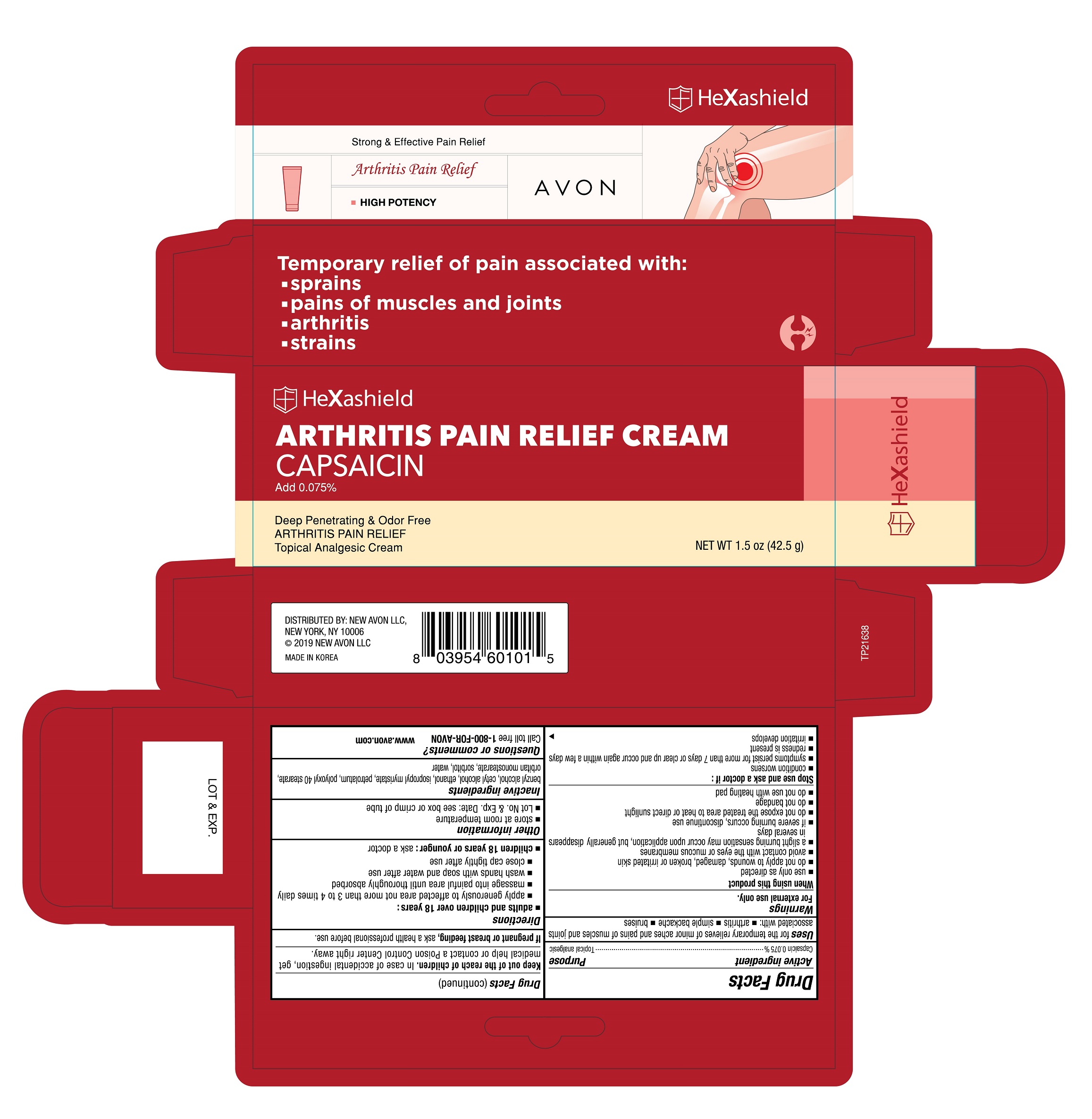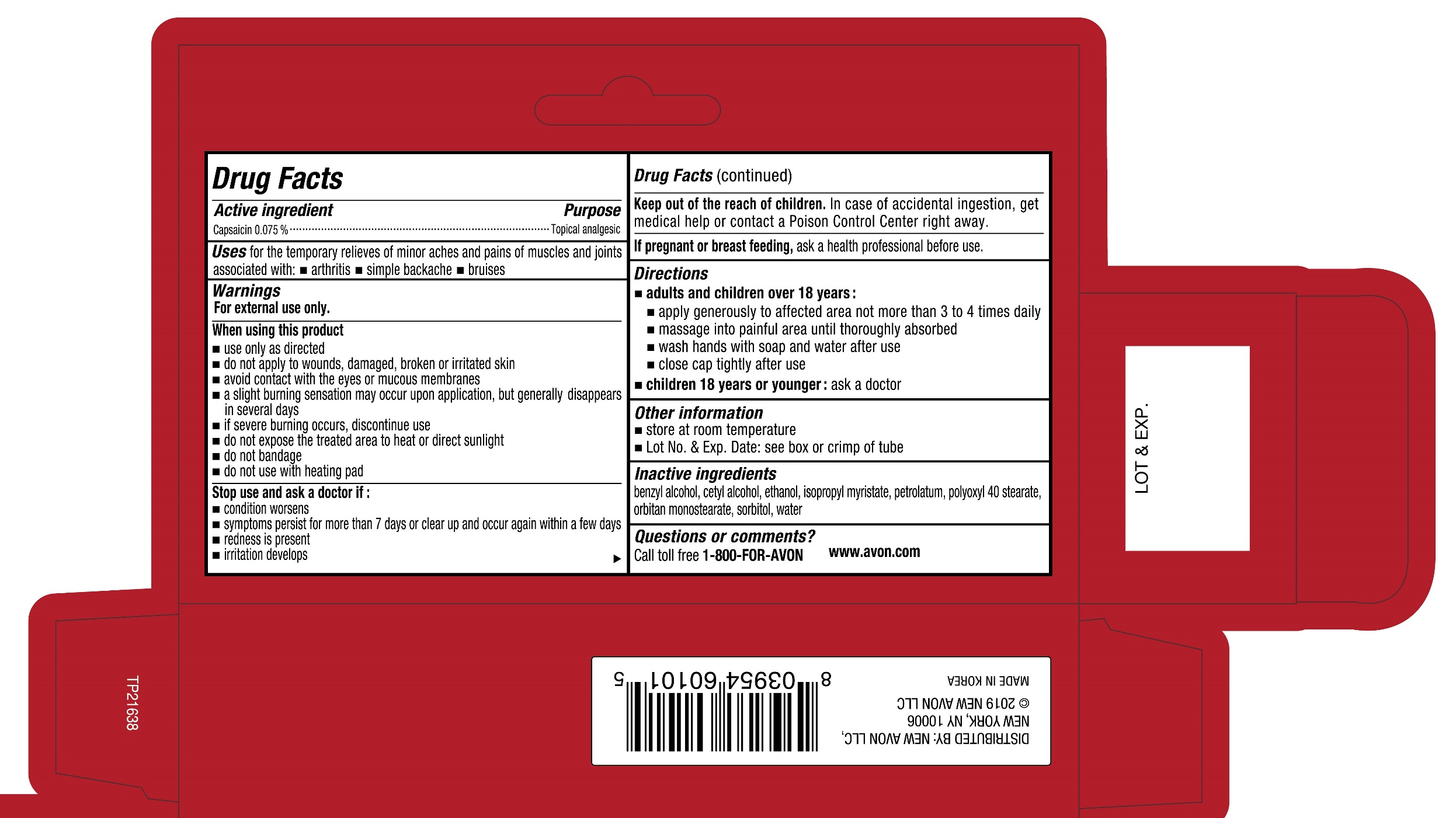 DRUG LABEL: AVON HeXashield Arthritis Pain Relief
NDC: 43136-101 | Form: CREAM
Manufacturer: Tai Guk Pharm. Co., Ltd.
Category: otc | Type: HUMAN OTC DRUG LABEL
Date: 20250101

ACTIVE INGREDIENTS: CAPSAICIN 0.75 mg/1 g
INACTIVE INGREDIENTS: SORBITOL; WATER; PETROLATUM; BENZYL ALCOHOL; ALCOHOL; POLYOXYL 40 STEARATE; SORBITAN MONOSTEARATE; CETYL ALCOHOL; ISOPROPYL MYRISTATE

AVON HeXashield Arthritis Pain Relief Cream Capsaicin

Active Ingredient

Capsaicin 0.075 %

Purpose

Topical analgesic

Uses

for temporary relieves of minor aches and pains of muscles and joints associated with:

- arthritis
- simple backache
- bruises

Warnings

For external use only.

When using this product

- use only as directed
- do not apply to wounds, damaged, broken or irritated skin
- avoid contact with the eyes or mucous membranes
- a slight burning sensation may occur upon application, but generally disappears in several days
- if severe burning occurs, discontinue use
- do not expose the treated area to heat or direct sunlight
- do not banage
- do not use with heating pad

Stop use and ask a doctor if :

- condition worsens
- symptoms persist for more than 7 days or clear up and occur again within a few days
- redness is present
- irritation develops

Keep out of reach of children.

In case of accidental ingestion, get medical help or contact a Poison Control Center right away.

Directions

- adults and children over 18 years:
  - apply generously to affected area not more than 3 to 4 times daily
- massage into painful area until thoroughly absorbed
- wash hands with soap and water after use
- close cap tightly after use
- children 18 years or younger :ask a doctor

Other information

- store at room temperature
- Lot No. & Exp. Date: see box or see crimp of tube

Inactive Ingredients

benzyl alcohol, cetyl alcohol, ethanol, isopropyl myristate, petrolatum, polyoxyl 40 stearate, orbitan monostearate, sorbitol, water

Questions or comments?

Call toll free 1-800-FOR-AVON

www.avon.com

Principal Display Panel

Strong & Effective Pain Relief

Arthritis Pain Relief

High Potency

AVON

Temporary relief of pain associated with:

- sprains
- pains of muscles and joints
- arthritis
- strains

HeXashield

ARTHRITIS PAIN RELIEF CREAM

CAPSAICIN

Add 0.075%

Deep Penetratng & Odor Free

ARTHRITIS PAIN RELIEF

Topical Analgesic Cream

NET WT 1.5 oz (43.5 g)